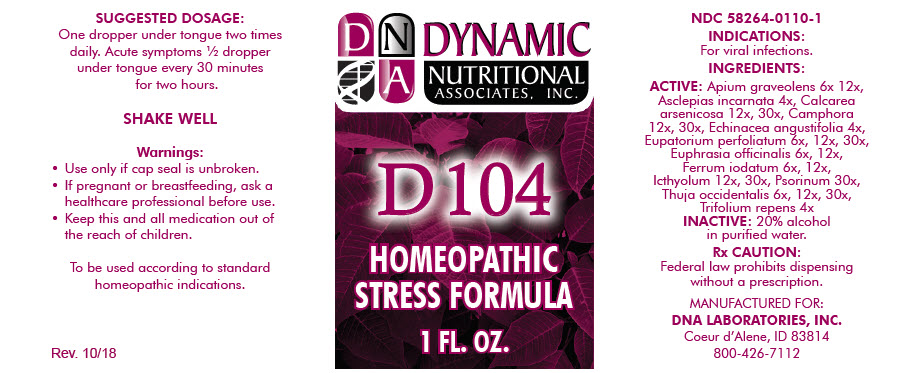 DRUG LABEL: D-104
NDC: 58264-0110 | Form: SOLUTION
Manufacturer: DNA Labs, Inc.
Category: homeopathic | Type: HUMAN OTC DRUG LABEL
Date: 20250113

ACTIVE INGREDIENTS: APIUM GRAVEOLENS WHOLE 6 [hp_X]/1 mL; ASCLEPIAS INCARNATA ROOT 4 [hp_X]/1 mL; CALCIUM ARSENATE 12 [hp_X]/1 mL; CAMPHOR (NATURAL) 12 [hp_X]/1 mL; ECHINACEA ANGUSTIFOLIA 4 [hp_X]/1 mL; EUPATORIUM PERFOLIATUM FLOWERING TOP 6 [hp_X]/1 mL; EUPHRASIA STRICTA 6 [hp_X]/1 mL; FERROUS IODIDE 6 [hp_X]/1 mL; ICHTHAMMOL 12 [hp_X]/1 mL; SCABIES LESION LYSATE (HUMAN) 30 [hp_X]/1 mL; THUJA OCCIDENTALIS LEAFY TWIG 6 [hp_X]/1 mL; TRIFOLIUM REPENS FLOWER 4 [hp_X]/1 mL
INACTIVE INGREDIENTS: ALCOHOL; WATER

D-104

NDC 58264-0110-1

INDICATIONS

PURPOSE

For viral infections.

INGREDIENTS

ACTIVE

Apium graveolens 6x 12x, Asclepias incarnata 4x, Calcarea arsenicosa 12x, 30x, Camphora 12x, 30x, Echinacea angustifolia 4x, Eupatorium perfoliatum 6x, 12x, 30x, Euphrasia officinalis 6x, 12x, Ferrum iodatum 6x, 12x, Icthyolum 12x, 30x, Psorinum 30x, Thuja occidentalis 6x, 12x, 30x, Trifolium repens 4x

INACTIVE

20% alcohol in purified water.

Rx CAUTION

Federal law prohibits dispensing without a prescription.

SUGGESTED DOSAGE

One dropper under tongue two times daily. Acute symptoms ½ dropper under tongue every 30 minutes for two hours.

STORAGE AND HANDLING

SHAKE WELL

Warnings

- Use only if cap seal is unbroken.

PREGNANCY OR BREAST FEEDING

- If pregnant or breastfeeding, ask a healthcare professional before use.

KEEP OUT OF REACH OF CHILDREN

- Keep this and all medication out of the reach of children.

To be used according to standard homeopathic indications.

PRINCIPAL DISPLAY PANEL - 1 FL. OZ. Bottle Label

DYNAMIC
NUTRITIONAL
ASSOCIATES, INC.

D 104

HOMEOPATHIC
STRESS FORMULA

1 FL. OZ.